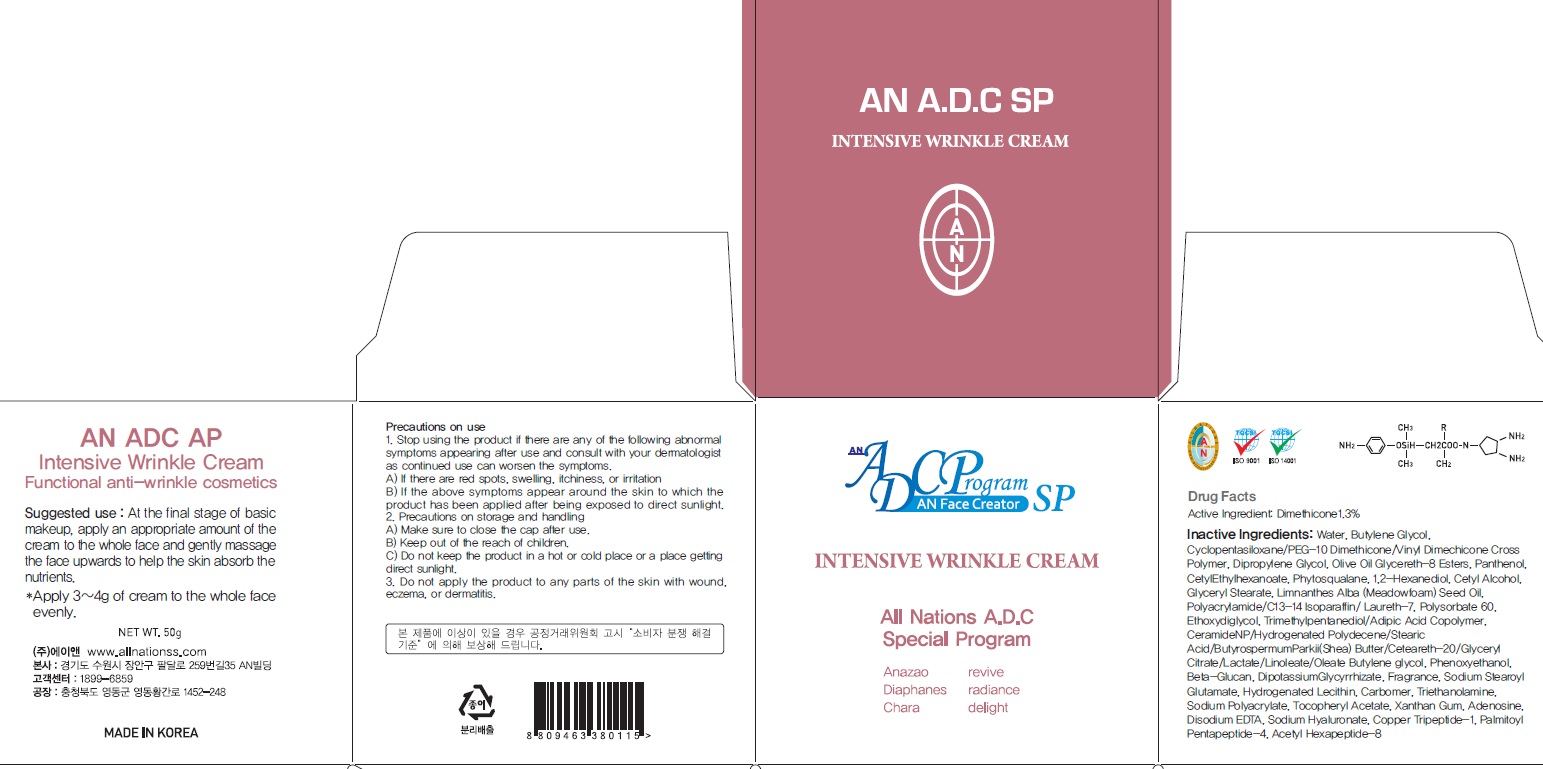 DRUG LABEL: AN ADC SP INTENSIVE WRINKLE
NDC: 69153-100 | Form: CREAM
Manufacturer: AN Co Ltd.
Category: otc | Type: HUMAN OTC DRUG LABEL
Date: 20160624

ACTIVE INGREDIENTS: Dimethicone 0.65 g/50 g
INACTIVE INGREDIENTS: Water; Butylene Glycol

ACTIVE INGREDIENT

Active Ingredient: Dimethicone 1.3%

INACTIVE INGREDIENT

Inactive Ingredients: Water, Butylene Glycol, Cyclopentasiloxane/PEG-10 Dimethicone/Vinyl Dimechicone Cross Polymer, Dipropylene Glycol, Olive Oil Glycereth-8 Esters, Panthenol, Cetyl Ethylhexanoate, Phytosqualane, 1,2-Hexanediol, Cetyl Alcohol, Glyceryl Stearate, Limnanthes Alba (Meadowfoam) Seed Oil, Polyacrylamide/C13-14 Isoparaffin/ Laureth-7, Polysorbate 60, Ethoxydiglycol, Trimethylpentanediol/Adipic Acid Copolymer, CeramideNP/Hydrogenated Polydecene/Stearic Acid/ButyrospermumParkii(Shea) Butter/Ceteareth-20/Glyceryl Citrate/Lactate/Linoleate/Oleate Butylene glycol, Phenoxyethanol, Beta-Glucan, Dipotassium Glycyrrhizate, Fragrance, Sodium Stearoyl Glutamate, Hydrogenated Lecithin, Carbomer, Triethanolamine, Sodium Polyacrylate, Tocopheryl Acetate, Xanthan Gum, Adenosine, Disodium EDTA, Sodium Hyaluronate, Copper Tripeptide-1, Palmitoyl Pentapeptide-4, Acetyl Hexapeptide-8

PURPOSE

Purpose: Skin Protectant

WARNINGS

Precautions on use: 1. Stop using the product if there are any of the following abnormal symptoms appearing after use and consult with your dermatologist as continued use can worsen the symptoms. A) If there are red spots, swelling, itchiness, or irritation B) If the above symptoms appear around the skin to which the product has been applied after being exposed to direct sunlight. 2. Precautions on storage and handling A) Make sure to close the cap after use. B) Keep out of the reach of children. C) Do not keep the product in a hot or cold place or a place getting direct sunlight. 3. Do not apply the product to any parts of the skin with wound, eczema, or dermatitis.

KEEP OUT OF REACH OF CHILDREN

Suggested use

Suggested use: At the final stage of basic makeup, apply an appropriate amount of the cream to the whole face and gently massage the face upwards to help the skin absorb the nutrients.

DOSAGE & ADMINISTRATION

Dosage & administration: Apply 3~4g of cream to the whole face evenly.